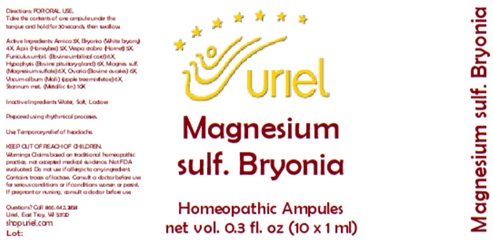 DRUG LABEL: Magnesium sulf. Bryonia
NDC: 48951-7216 | Form: LIQUID
Manufacturer: Uriel Pharmacy Inc.
Category: homeopathic | Type: HUMAN OTC DRUG LABEL
Date: 20250430

ACTIVE INGREDIENTS: ARNICA MONTANA 3 [hp_X]/1 mL; SUS SCROFA UMBILICAL CORD 6 [hp_X]/1 mL; BRYONIA ALBA ROOT 4 [hp_X]/1 mL; APIS MELLIFERA 5 [hp_X]/1 mL; VESPA CRABRO 5 [hp_X]/1 mL; BOS TAURUS OVARY 6 [hp_X]/1 mL; VISCUM ALBUM FRUITING TOP 6 [hp_X]/1 mL; MAGNESIUM SULFATE, UNSPECIFIED 6 [hp_X]/1 mL; BOS TAURUS PITUITARY GLAND 6 [hp_X]/1 mL; TIN 10 [hp_X]/1 mL
INACTIVE INGREDIENTS: SODIUM CHLORIDE; LACTOSE, UNSPECIFIED FORM; WATER

Magnesium sulf. Bryonia

INDICATIONS AND USAGE

Directions: FOR ORAL USE.

DOSAGE AND ADMINISTRATION

Take the contents of one ampule under the tongue and hold for 30 seconds, then swallow.

Inactive Ingredients: Water, Salt, Lactose

Prepared using rhythmical processes.

PURPOSE

Use: Temporary relief of headache.

KEEP OUT OF REACH OF CHILDREN.

WARNINGS

Warnings: Claims based on traditional homeopathic practice, not accepted medical evidence. Not FDA evaluated. Do not use if allergic to any ingredient. Contains traces of lactose. Consult a doctor before use for serious conditions or if conditions worsen or persist. If pregnant or nursing, consult a doctor before use.

Questions? Call 866.642.2858
Uriel, East Troy, WI 53120
shopuriel.com Lot:

ACTIVE INGREDIENT

Active Ingredients: Arnica 3X, Bryonia (White bryony) 4X, Apis (Honeybee) 5X, Vespa crabro (Hornet) 5X, Funiculus umbil. (Bovine umbilical cord) 6X, Hypophysis (Bovine pituitary gland) 6X, Magnes. sulf. (Magnesium sulfate) 6X, Ovaria (Bovine ovaries) 6X, Viscum album (Mali) (apple tree mistletoe) 6X, Stannum met. (Metallic tin) 10X